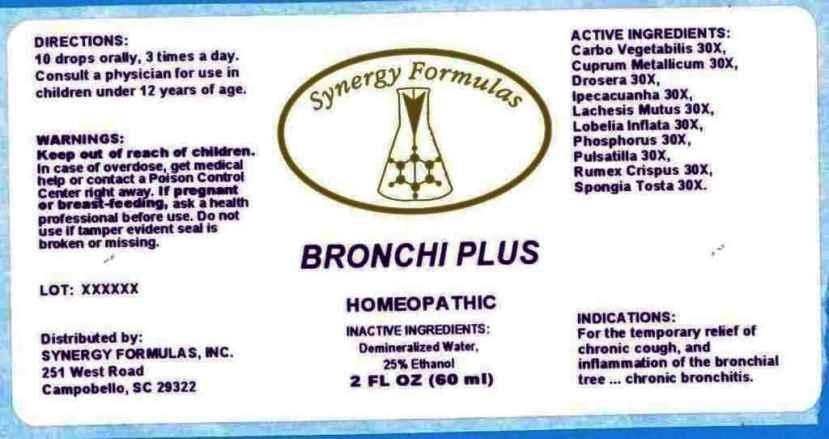 DRUG LABEL: Bronchi Plus
NDC: 43772-0017 | Form: LIQUID
Manufacturer: Synergy Formulas, Inc.
Category: homeopathic | Type: HUMAN OTC DRUG LABEL
Date: 20140825

ACTIVE INGREDIENTS: ACTIVATED CHARCOAL 30 [hp_X]/1 mL; COPPER 30 [hp_X]/1 mL; DROSERA ROTUNDIFOLIA 30 [hp_X]/1 mL; IPECAC 30 [hp_X]/1 mL; LACHESIS MUTA VENOM 30 [hp_X]/1 mL; LOBELIA INFLATA 30 [hp_X]/1 mL; PHOSPHORUS 30 [hp_X]/1 mL; PULSATILLA VULGARIS 30 [hp_X]/1 mL; RUMEX CRISPUS ROOT 30 [hp_X]/1 mL; SPONGIA OFFICINALIS SKELETON, ROASTED 30 [hp_X]/1 mL
INACTIVE INGREDIENTS: WATER; ALCOHOL

DRUG FACTS

ACTIVE INGREDIENTS:

Carbo Vegetabilis 30X, Cuprum Metallicum 30X, Drosera (Rotundifolia) 30X, Ipecacuanha 30X, Lachesis Mutus 30X, Lobelia Inflata 30X, Phosphorus 30X, Pulsatilla (Vulgaris) 30X, Rumex Crispus 30X, Spongia Tosta 30X

INDCIATIONS:

For the temporary relief of chronic cough, and inflammation of the bronchial tree...chronic bronchitis.

WARNINGS:

Keep out of reach of children. In case of overdose, get medical help or contact a Poison Control Center right away.

If pregnant or breast-feeding, ask a health professional before use.

Do not use if tamper evident seal is broken or missing.

Keep out of reach of children. In case of overdose, get medical help or contact a Poison Control Center right away.

DIRECTIONS:

10 drops orally, 3 times a day. Consult a physician for use in children under 12 years of age.

INDCIATIONS:

For the temporary relief of chronic cough, and inflammation of the bronchial tree...chronic bronchitis.

INACTIVE INGREDIENTS:

Demineralized Water, 25% Ethanol.

QUESTIONS:

Distributed by:

SYNERGY FORMULAS, INC.

251 West Road

Campobello, SC 29322

PACKAGE LABEL DISPLAY

Synergy Formulas

BRONCHI PLUS

HOMEOPATHIC

2 FL OZ (60 ml)